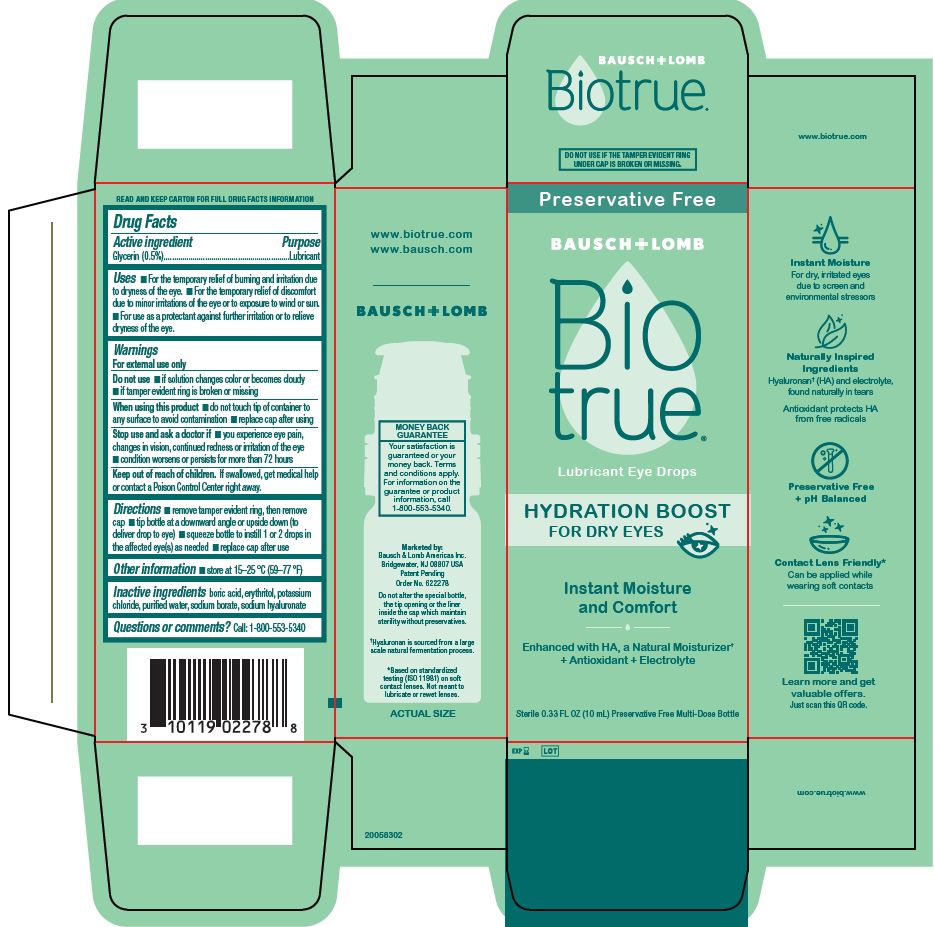 DRUG LABEL: Biotrue Hydration Boost
NDC: 24208-006 | Form: SOLUTION/ DROPS
Manufacturer: Bausch & Lomb Incorporated
Category: otc | Type: HUMAN OTC DRUG LABEL
Date: 20250519

ACTIVE INGREDIENTS: GLYCERIN 5 mg/1 mL
INACTIVE INGREDIENTS: BORIC ACID; ERYTHRITOL; POTASSIUM CHLORIDE; SODIUM BORATE; HYALURONATE SODIUM; WATER

Drug Facts

Active ingredient

Glycerin (0.5%)

Purpose

Lubricant

Uses

- For the temporary relief of burning and irritation due to dryness of the eye.
- For the temporary relief of discomfort due to minor irritations of the eye or to exposure to wind or sun.
- For use as a protectant against further irritation or to relieve dryness of the eye.

Warnings

For external use only

Do not use

- if solution changes color or becomes cloudy
- if tamper evident ring is broken or missing

When using this product

- do not touch tip of container to any surface to avoid contamination
- replace cap after using

Stop use and ask a doctor if

- you experience eye pain, changes in vision, continued redness or irritation of the eye
- condition worsens or persists for more than 72 hours

Keep out of reach of children.

If swallowed, get medical help or contact a Poison Control Center right away.

Directions

- remove tamper evident ring, then remove cap
- tip bottle at a downward angle or upside down (to deliver drop to eye)
- squeeze bottle to instill 1 or 2 drops in the affected eye(s) as needed
- replace cap after use

Other Information

- store at 15—25 °C (59—77 °F)

Inactive ingredients

boric acid, erythritol, potassium chloride, purified water, sodium borate, sodium hyaluronate

Questions or comments?

Call: 1-800-553-5340

Package/Label Principal Display Panel

Preservative Free
BAUSCH + LOMB

Bio
true®

Lubricant Eye Drops

HYDRATION BOOST
FOR DRY EYES [EYE IMAGE]
Instant Moisture
and Comfort

Enhanced with HA, a Natural Moisturizer†
+ Antioxidant + Electrolyte

Sterile - 0.33 FL OZ (10 mL) Preservative Free Multi-Dose Bottle

20058302